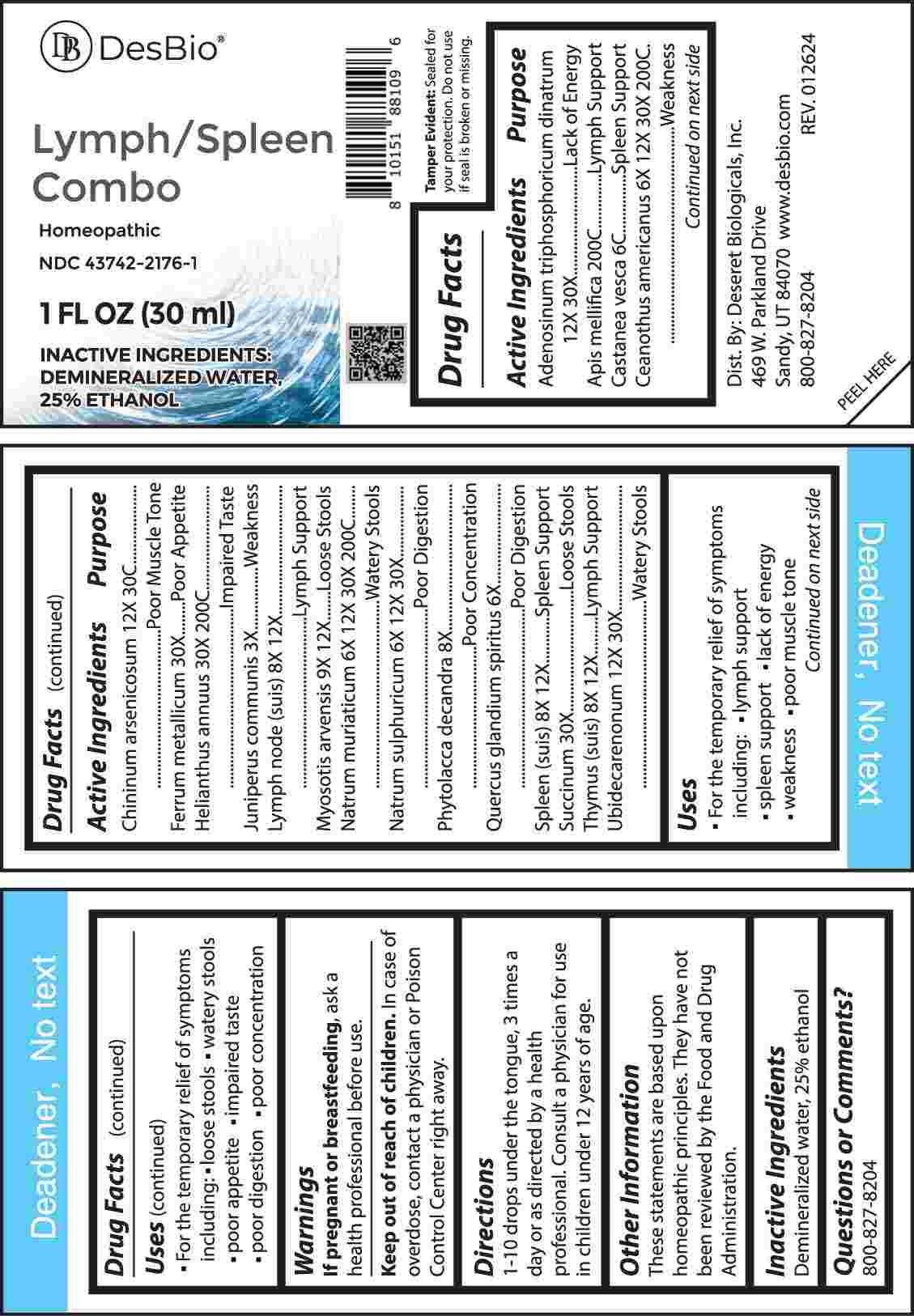 DRUG LABEL: Lymph/Spleen Combo
NDC: 43742-2176 | Form: LIQUID
Manufacturer: Deseret Biologicals, Inc.
Category: homeopathic | Type: HUMAN OTC DRUG LABEL
Date: 20240731

ACTIVE INGREDIENTS: ADENOSINE TRIPHOSPHATE DISODIUM 12 [hp_X]/1 mL; APIS MELLIFERA 200 [hp_C]/1 mL; CASTANEA SATIVA LEAF 6 [hp_C]/1 mL; CEANOTHUS AMERICANUS LEAF 6 [hp_X]/1 mL; QUININE ARSENITE 12 [hp_X]/1 mL; IRON 30 [hp_X]/1 mL; HELIANTHUS ANNUUS FLOWERING TOP 30 [hp_X]/1 mL; JUNIPER BERRY 3 [hp_X]/1 mL; SUS SCROFA LYMPH 8 [hp_X]/1 mL; MYOSOTIS ARVENSIS WHOLE 9 [hp_X]/1 mL; SODIUM CHLORIDE 6 [hp_X]/1 mL; SODIUM SULFATE 6 [hp_X]/1 mL; PHYTOLACCA AMERICANA ROOT 8 [hp_X]/1 mL; QUERCUS ROBUR NUT 6 [hp_X]/1 mL; SUS SCROFA SPLEEN 8 [hp_X]/1 mL; AMBER 30 [hp_X]/1 mL; SUS SCROFA THYMUS 8 [hp_X]/1 mL; UBIDECARENONE 12 [hp_X]/1 mL
INACTIVE INGREDIENTS: WATER; ALCOHOL

DRUG FACTS:

ACTIVE INGREDIENTS:

Adenosinum Triphosphoricum Dinatrum 12X, 30X, Apis Mellifica 200C, Castanea Vesca 6C, Ceanothus Americanus 6X, 12X, 30X, 200C, Chininum Arsenicosum 12X, 30C, Ferrum Metallicum 30X, Helianthus Annuus 30X, 200C, Juniperus Communis 3X, Lymph Node (Suis) 8X, 12X, Myosotis Arvensis 9X, 12X, Natrum Muriaticum 6X, 12X, 30X, 200C, Natrum Sulphuricum 6X, 12X, 30X, Phytolacca Decandra 8X, Quercus Glandium Spiritus 6X, Spleen (Suis) 8X, 12X, Succinum 30X, Thymus (Suis) 8X, 12X, Ubidecarenonum 12X, 30X.

PURPOSE:

Adenosinum Triphosphoricum Dinatrum – Lack of Energy, Apis Mellifica – Lymph Support, Castanea Vesca – Spleen Support, Ceanothus Americanus - Weakness, Chininum Arsenicosum – Poor Muscle Tone, Ferrum Metallicum – Poor Appetite, Helianthus Annuus – Impaired Taste, Juniperus Communis - Weakness, Lymph Node (Suis) – Lymph Support, Myosotis Arvensis – Loose Stools, Natrum Muriaticum – Watery Stools, Natrum Sulphuricum – Poor Digestion, Phytolacca Decandra – Poor Concentration, Quercus Glandium Spiritus – Poor Digestion, Spleen (Suis) – Spleen Support, Succinum – Loose Stools, Thymus (Suis) – Lymph Support, Ubidecarenonum – Watery Stools

USES:

• For the temporary relief of symptoms including:

• lymph support • spleen support • lack of energy

• weakness • poor muscle tone • loose stools

• watery stools • poor appetite • impaired taste

• poor digestion • poor concentration

These statements are based upon homeopathic principles. They have not been reviewed by the Food and Drug Administration.

WARNINGS:

If pregnant or breast-feeding, ask a health professional before use.

Keep out of reach of children. In case of overdose, contact a physician or Poison Control Center right away.

Tamper Evident: Sealed for your protection. Do not use if seal is broken or missing.

KEEP OUT OF REACH OF CHILDREN:

In case of overdose, contact a physician or Poison Control Center right away.

DIRECTIONS:

1-10 drops under the tongue, 3 times a day or as directed by a health professional. Consult a physician for use in children under 12 years of age.

INACTIVE INGREDIENTS:

Demineralized water, 25% ethanol

QUESTIONS:

Dist. By: Deseret Biologicals, Inc.
469 W. Parkland Drive
Sandy, UT 84070

www.desbio.com

800-827-8204

PACKAGE LABEL DISPLAY:

DesBio

Lymph/Spleen

Combo

Homeopathic
NDC 43742-2176-1
1 FL OZ (30 ml)